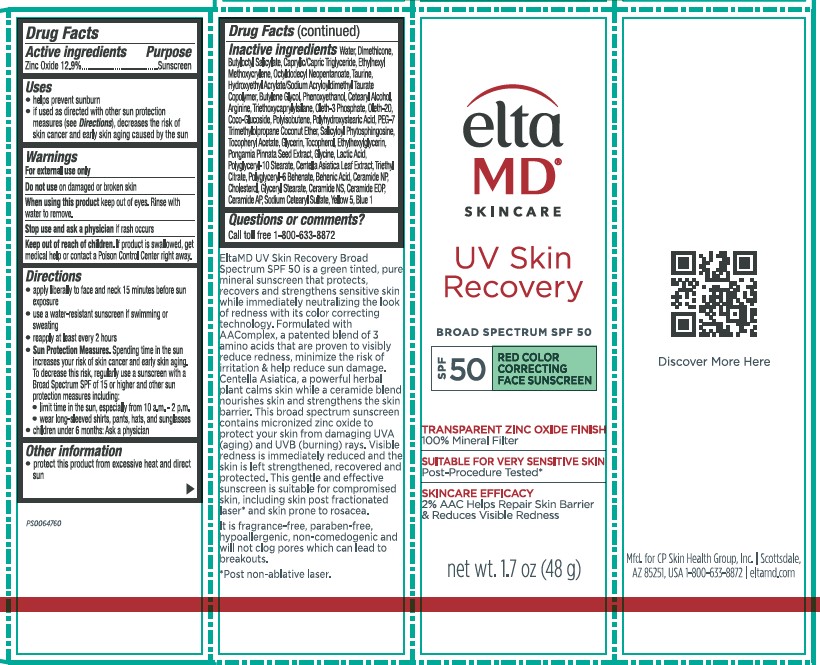 DRUG LABEL: UV Skin Recovery SPF 50 Red Correcting
NDC: 72043-0334 | Form: LOTION
Manufacturer: CP Skin Health Group, Inc.
Category: otc | Type: HUMAN OTC DRUG LABEL
Date: 20241204

ACTIVE INGREDIENTS: ZINC OXIDE 12.9 g/100 g
INACTIVE INGREDIENTS: POLYGLYCERYL-6 BEHENATE; TRIETHOXYCAPRYLYLSILANE; OLETH-3 PHOSPHATE; TOCOPHEROL; OCTYLDODECYL NEOPENTANOATE; TAURINE; GLYCINE; WATER; BUTYLENE GLYCOL; PHENOXYETHANOL; PEG-7 TRIMETHYLOLPROPANE COCONUT ETHER; .ALPHA.-TOCOPHEROL ACETATE; ETHYLHEXYLGLYCERIN; CERAMIDE AP; CERAMIDE NP; GLYCERYL STEARATE; POLYGLYCERYL-10 STEARATE; BLUE 1; YELLOW 5; HYDROXYETHYL ACRYLATE/SODIUM ACRYLOYLDIMETHYL TAURATE COPOLYMER (100000 MPA.S AT 1.5%); ARGININE; OLETH-20; CENTELLA ASIATICA LEAF; CITRIC ACID; BEHENIC ACID; CHOLESTEROL; CERAMIDE NS; SALICYLOYL PHYTOSPHINGOSINE; SODIUM CETEARYL SULFATE; CERAMIDE 1 A; BUTYLOCTYL SALICYLATE; DIMETHICONE; TRIETHYL CITRATE; HYDROGENATED POLYISOBUTENE (1300 MW); GLYCERIN; PONGAMIA PINNATA SEED EXTRACT; CETEARYL ALCOHOL; ETHYLHEXYL METHOXYCRYLENE; CAPRYLIC/CAPRIC TRIGLYCERIDE; POLYHYDROXYSTEARIC ACID (2300 MW); COCO-GLUCOSIDE; LACTIC ACID

Elta MD UV Skin Recovery SPF 50 Red Correcting

Drug Facts

ACTIVE INGREDIENT

Zinc Oxide (12.9%)

PURPOSE

Sunscreen

INDICATIONS AND USAGE

helps prevent sunburn
if used as directed with other sun protection measures (see Directions), decreases the risk of skin cancer and early skin aging caused by the sun

WARNINGS

For external use only

Do not use on damged or broken skin

When using this product keep out of eyes. Rinse with water to remove

Stop use and ask a physician if rash occurs

Keep out of reach of children. If product is swallowed, get medical help or contact Poison Control Center right away.

DOSAGE AND ADMINISTRATION

apply liberally to face and neck 15 minutes before sun exposure
use a water-resistant sunscreen if swimming or sweating
reapply at least every 2 hours
Sun Protection Measures. Spending time in the sun increases your risk of skin cancer and early skin aging.
To decrease risk, regularly use a sunscreen with a Broad Spectrum SPF of 15 or higher and other sun protection measures including: limit time in the sun, especially from 10a.m.-2p .m.

wear long-sleeved shirls, pants, hats, and sunglasses

children under 6 months: Ask a physicianician

STORAGE AND HANDLING

protect this product from excessive heat and direct sun

INACTIVE INGREDIENT

Water, Dimethicone, Butyloctyl Salicylate, Caprylic/Capric Triglyceride, Ethylhexyl Methoxycrylene, Octyldodecyl Neopentanoate, Taurine, Hydroxyethyl Acrylate/Sodium Acryloyldimethyl Taurate Copolymer, Butylene Glycol, Phenoxyethanol, Cetearyl Alcohol, Arginine, Triethoxycaprylylsilane, Oleth-20, Oleth-3 Phosphate, Coco-Glucoside, Polyisobutene, Citric Acid, Polyhydroxystearic
Acid, PEG-7 Trimethylolpropane Coconut Ether, Salicyloyl Phytosphingosine, Tocopheryl Acetate, Glycerin, Tocopherol,
Ethylhexylglycerin, Sorbitan Isostearate, Pongamia Pinnata Seed Extract, Glycine, Yellow 5, Lactic Acid, Polyglyceryl-10 Stearate,
Centella Asiatica Leaf Extract, Blue 1, Glucose, Triethyl Citrate, Polyglyceryl-6 Behenate, Behenic Acid, Ceramide NP,
Cholesterol, Glyceryl Stearate, Ceramide NS, Ceramide EOP, Ceramide AP.

QUESTIONS

Call toll free 1-800-633-8872